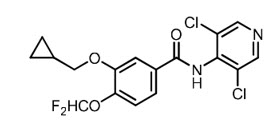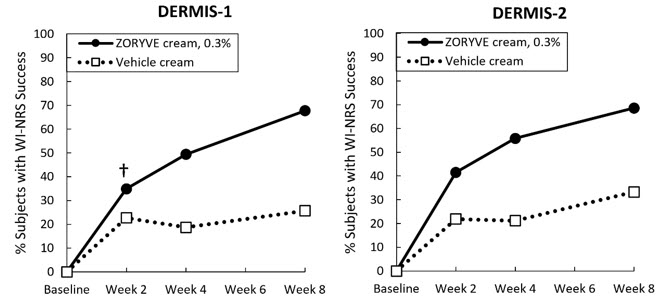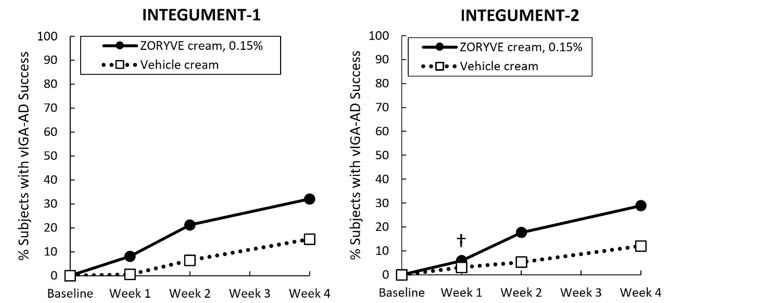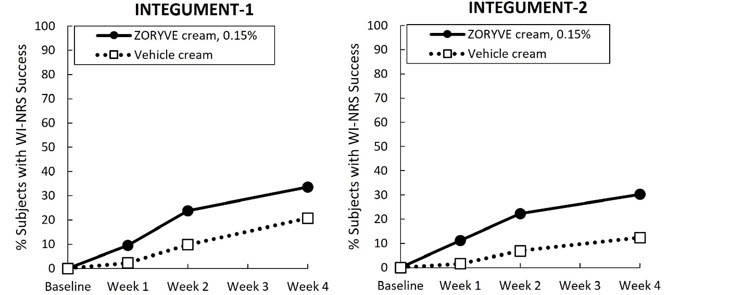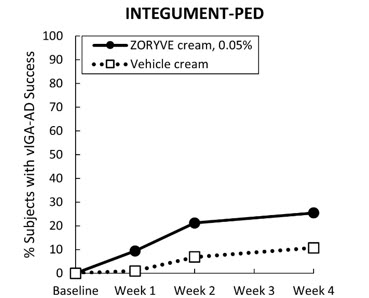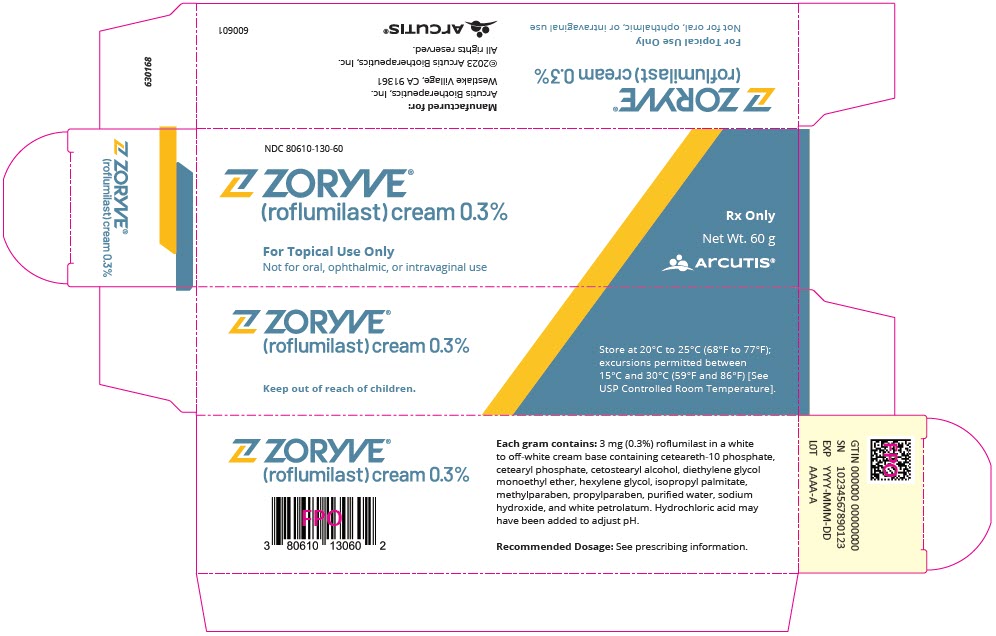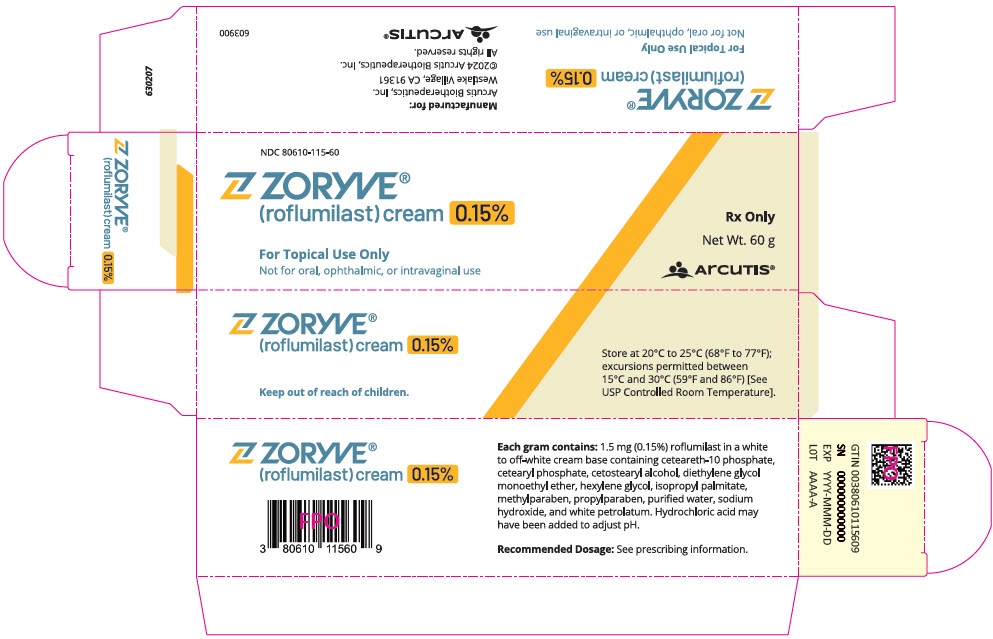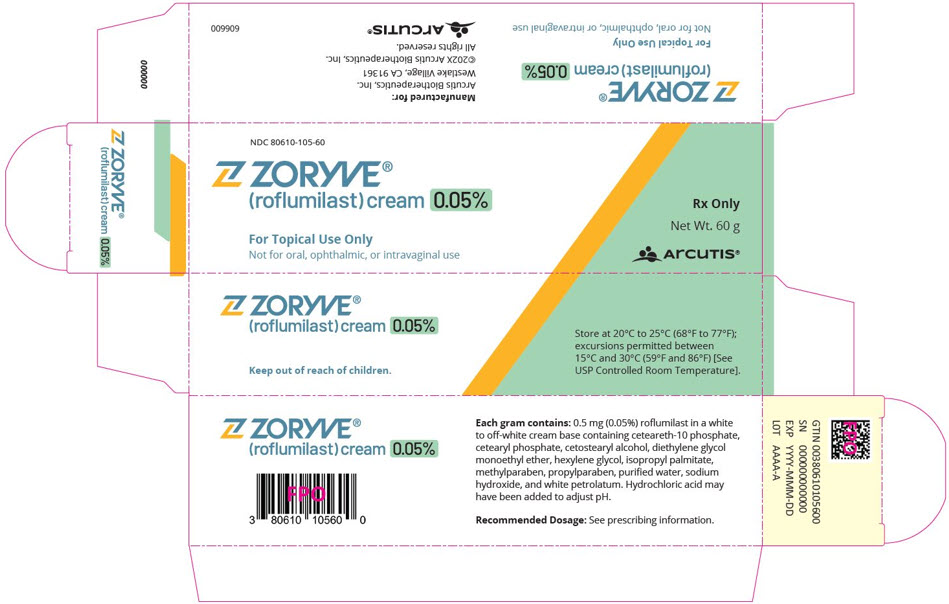 DRUG LABEL: ZORYVE
NDC: 80610-130 | Form: CREAM
Manufacturer: Arcutis Biotherapeutics, Inc.
Category: prescription | Type: HUMAN PRESCRIPTION DRUG LABEL
Date: 20260130

ACTIVE INGREDIENTS: ROFLUMILAST 3 mg/1 g
INACTIVE INGREDIENTS: CETEARETH-10 PHOSPHATE; CETOSTEARYL ALCOHOL; CETEARYL PHOSPHATE; DIETHYLENE GLYCOL MONOETHYL ETHER; HEXYLENE GLYCOL; ISOPROPYL PALMITATE; METHYLPARABEN; PROPYLPARABEN; WATER; SODIUM HYDROXIDE; WHITE PETROLATUM; HYDROCHLORIC ACID

HIGHLIGHTS OF PRESCRIBING INFORMATION

These highlights do not include all the information needed to use ZORYVE cream safely and effectively. See full prescribing information for ZORYVE cream.
ZORYVE® (roflumilast) cream 0.3%, 0.15%, 0.05%, for topical use
Initial U.S. Approval: 2011

RECENT MAJOR CHANGES

Indications and Usage, Atopic Dermatitis (1.2) | 10/2025
Dosage and Administration (2) | 10/2025

1 INDICATIONS AND USAGE

ZORYVE cream is a phosphodiesterase 4 inhibitor:

Plaque Psoriasis

- ZORYVE cream, 0.3%, is indicated for the topical treatment of plaque psoriasis, including intertriginous areas, in adult and pediatric patients 6 years of age and older. (1.1)

Atopic Dermatitis

- ZORYVE cream, 0.15%, is indicated for the topical treatment of mild to moderate atopic dermatitis in adult and pediatric patients 6 years of age and older. (1.2)
- ZORYVE cream, 0.05%, is indicated for the topical treatment of mild to moderate atopic dermatitis in pediatric patients 2 to 5 years of age. (1.2)

2 DOSAGE AND ADMINISTRATION

- For topical use only. (2)
- Not for ophthalmic, oral, or intravaginal use. (2)

Plaque Psoriasis

- Apply ZORYVE cream, 0.3%, once daily to affected areas. (2)

Atopic Dermatitis

- Adult and Pediatric Patients 6 Years of Age and Older
  - Apply ZORYVE cream, 0.15%, once daily to affected areas. (2)
- Pediatric Patients 2 to 5 Years of Age
  - Apply ZORYVE cream, 0.05%, once daily to affected areas. (2)

3 DOSAGE FORMS AND STRENGTHS

- Cream, 0.3%: 3 mg of roflumilast per gram in 60-gram tubes. (3)
- Cream, 0.15%: 1.5 mg of roflumilast per gram in 60-gram tubes. (3)
- Cream, 0.05%: 0.5 mg of roflumilast per gram in 60-gram tubes. (3)

4 CONTRAINDICATIONS

Moderate to severe liver impairment (Child-Pugh B or C). (4)

6 ADVERSE REACTIONS

The most common adverse reactions (reported in ≥1% of subjects) are:

- Plaque Psoriasis: diarrhea, headache, insomnia, nausea, application site pain, upper respiratory tract infection, and urinary tract infection. (6.1)
- Atopic Dermatitis: headache, nausea, application site pain, diarrhea, vomiting, upper respiratory tract infection, rhinitis, and conjunctivitis. (6.1)

To report SUSPECTED ADVERSE REACTIONS, contact Arcutis Biotherapeutics, Inc. at 1-844-692-6729 or FDA at 1-800-FDA-1088 or www.fda.gov/medwatch.

7 DRUG INTERACTIONS

- Co-administration of roflumilast with systemic CYP3A4 inhibitors or dual inhibitors that inhibit both CYP3A4 and CYP1A2 simultaneously may increase roflumilast systemic exposure and may result in increased adverse reactions. If these products are co-administered with ZORYVE cream, weigh the potential for increased adverse reactions against benefit. (7.1)
- Co-administration of roflumilast with oral contraceptives containing gestodene and ethinyl estradiol may increase roflumilast systemic exposure and may result in increased adverse reactions. If these products are co-administered with ZORYVE cream, weigh the potential for increased adverse reactions against benefit. (7.1)

FULL PRESCRIBING INFORMATION

1 INDICATIONS AND USAGE

1.1 Plaque Psoriasis

ZORYVE® cream, 0.3%, is indicated for topical treatment of plaque psoriasis, including intertriginous areas, in adult and pediatric patients 6 years of age and older.

1.2 Atopic Dermatitis

ZORYVE cream, 0.15%, is indicated for topical treatment of mild to moderate atopic dermatitis in adult and pediatric patients 6 years of age and older.

ZORYVE cream, 0.05%, is indicated for topical treatment of mild to moderate atopic dermatitis in pediatric patients 2 to 5 years of age.

2 DOSAGE AND ADMINISTRATION

Plaque Psoriasis

- Use ZORYVE cream, 0.3%, for the treatment of plaque psoriasis in adult and pediatric patients 6 years of age and older.

Atopic Dermatitis

- Use ZORYVE cream, 0.15%, for the treatment of mild to moderate atopic dermatitis in adult and pediatric patients 6 years of age and older.
- Use ZORYVE cream, 0.05%, for the treatment of mild to moderate atopic dermatitis in pediatric patients 2 to 5 years of age.

Administration Instructions

- Apply ZORYVE cream to affected areas once daily and rub in completely. Wash hands after application.
- ZORYVE cream is for topical use only and not for ophthalmic, oral, or intravaginal use.

3 DOSAGE FORMS AND STRENGTHS

- Cream, 0.3%: 3 mg of roflumilast per gram of white to off-white cream in 60-gram tubes.
- Cream, 0.15%: 1.5 mg of roflumilast per gram of white to off-white cream in 60-gram tubes.
- Cream, 0.05%: 0.5 mg of roflumilast per gram of white to off-white cream in 60-gram tubes.

4 CONTRAINDICATIONS

ZORYVE cream is contraindicated in patients with moderate to severe liver impairment (Child-Pugh B or C) [see Use in Specific Populations (8.6), Clinical Pharmacology (12.3)].

6 ADVERSE REACTIONS

6.1 Clinical Trials Experience

Because clinical trials are conducted under widely varying conditions, adverse reaction rates observed in the clinical trials of a drug cannot be directly compared to rates in the clinical trials of another drug and may not reflect the rates observed in practice.

Plaque Psoriasis

Adult and Pediatric Subjects 6 Years of Age and Older

In two multicenter, randomized, double-blind, vehicle-controlled trials (DERMIS-1 and DERMIS-2), 881 adult and pediatric subjects 6 years of age or older with plaque psoriasis were treated with ZORYVE cream, 0.3%, or vehicle cream once daily for 8 weeks [see Clinical Studies (14.1)].

The proportion of subjects who discontinued treatment due to an adverse reaction was 1.0% for subjects treated with ZORYVE cream, 0.3%, and 1.3% for subjects treated with vehicle cream. The most common adverse reaction that led to discontinuation of ZORYVE cream, 0.3%, was application site urticaria (0.3%).

Table 1 presents adverse reactions that occurred in at least 1% of subjects treated with ZORYVE cream, 0.3%, and for which the rate exceeded the rate for vehicle cream.

Table 1: Adverse Reactions Reported in ≥1% of Adult and Pediatric Subjects 6 Years of Age and Older with Plaque Psoriasis Treated with ZORYVE Cream, 0.3%, (and More Frequently than Vehicle Cream) for 8 Weeks in Trials DERMIS-1 and DERMIS-2
Adverse Reaction | ZORYVE Cream, 0.3% (N=576) n (%) | Vehicle Cream (N=305) n (%)
Diarrhea | 18 (3.1) | 0 (0.0)
Headache | 14 (2.4) | 3 (1.0)
Insomnia | 8 (1.4) | 2 (0.7)
Nausea | 7 (1.2) | 1 (0.3)
Application site pain | 6 (1.0) | 1 (0.3)
Upper respiratory tract infection | 6 (1.0) | 1 (0.3)
Urinary tract infection | 6 (1.0) | 2 (0.7)

In 594 subjects with plaque psoriasis who continued treatment with ZORYVE cream, 0.3%, for up to 64 weeks in open-label extension trials, the adverse reaction profile was consistent with that observed in vehicle-controlled trials.

Atopic Dermatitis

Adult and Pediatric Subjects 6 Years of Age and Older

In two multicenter, randomized, double-blind, vehicle-controlled trials (INTEGUMENT-1 and INTEGUMENT-2), 1336 adult and pediatric subjects 6 years of age or older with mild to moderate atopic dermatitis were treated with ZORYVE cream, 0.15%, or vehicle cream once daily for 4 weeks [see Clinical Studies (14.2)].

The proportion of subjects who discontinued treatment due to an adverse reaction was 1.6% for subjects treated with ZORYVE cream, 0.15%, and 1.1% for subjects treated with vehicle cream.

Table 2 presents adverse reactions that occurred in at least 1% of subjects treated with ZORYVE cream, 0.15%, and for which the rate exceeded the rate for vehicle cream.

Table 2: Adverse Reactions Reported in ≥1% of Adult and Pediatric Subjects 6 Years of Age and Older with Atopic Dermatitis Treated with ZORYVE Cream, 0.15%, (and More Frequently than Vehicle Cream) for 4 Weeks in Trials INTEGUMENT-1 and INTEGUMENT-2
Adverse Reaction | ZORYVE Cream, 0.15% (N=885) n (%) | Vehicle Cream (N=451) n (%)
Headache | 26 (2.9) | 4 (0.9)
Nausea | 17 (1.9) | 2 (0.4)
Application site pain | 13 (1.5) | 3 (0.7)
Diarrhea | 13 (1.5) | 2 (0.4)
Vomiting | 13 (1.5) | 2 (0.4)

The adverse reaction of insomnia was reported in fewer than 1% of subjects treated with ZORYVE cream, 0.15%.

Pediatric Subjects 2 to 5 Years of Age

In a multicenter, randomized, double-blind, vehicle-controlled trial (INTEGUMENT-PED), 652 pediatric subjects 2 to 5 years of age with mild to moderate atopic dermatitis were treated with ZORYVE cream, 0.05%, or vehicle cream once daily for 4 weeks [see Clinical Studies (14.2)].

Table 3 presents adverse reactions that occurred in at least 1% of subjects treated with ZORYVE cream, 0.05%, and for which the rate exceeded the rate for vehicle cream.

Table 3: Adverse Reactions Reported in ≥1% of Pediatric Subjects 2 to 5 Years of Age with Atopic Dermatitis Treated with ZORYVE Cream, 0.05%, (and More Frequently than Vehicle) for 4 Weeks in Trial INTEGUMENT-PED
Adverse Reaction | ZORYVE Cream, 0.05% N=437 n (%) | Vehicle Cream N=215 n (%)
Upper respiratory tract infection | 18 (4.1) | 3 (1.4)
Diarrhea | 11 (2.5) | 1 (0.5)
Vomiting | 9 (2.1) | 0
Rhinitis | 7 (1.6) | 0
Conjunctivitis | 6 (1.4) | 0
Headache | 5 (1.1) | 0

Adult and Pediatric Subjects 2 Years of Age and Older

The long-term safety of ZORYVE cream, 0.15%, and ZORYVE cream, 0.05%, was assessed in an open-label extension trial of 1219 subjects 2 years of age and older with mild to moderate atopic dermatitis who had completed one of the 4-week vehicle-controlled trials. The safety profile observed in the open-label extension trial was generally consistent with the safety profile observed at Week 4.

7 DRUG INTERACTIONS

7.1 Effects of Other Drugs on ZORYVE Cream

Drugs that Inhibit Cytochrome P450 (CYP) Enzymes

No formal drug-drug interaction studies were conducted with ZORYVE cream; however, the co-administration of roflumilast with systemic CYP3A4 inhibitors or dual inhibitors that inhibit both CYP3A4 and CYP1A2 simultaneously may increase roflumilast systemic exposure and may result in increased adverse reactions. If these products are co-administered with ZORYVE cream, weigh the potential for increased adverse reactions against benefit [see Clinical Pharmacology (12.3)].

Oral Contraceptives Containing Gestodene and Ethinyl Estradiol

The co-administration of roflumilast with oral contraceptives containing gestodene and ethinyl estradiol may increase roflumilast systemic exposure and may result in increased adverse reactions. If these products are co-administered with ZORYVE cream, weigh the potential for increased adverse reactions against benefit [see Clinical Pharmacology (12.3)].

8 USE IN SPECIFIC POPULATIONS

8.1 Pregnancy

Risk Summary

There are insufficient data available on the use of ZORYVE cream in pregnant women to inform a drug-associated risk of major birth defects, miscarriage, or other adverse maternal or fetal outcomes. In animal reproduction studies, roflumilast administered orally to pregnant rats and rabbits during the period of organogenesis produced no fetal structural abnormalities at doses up to 36 and 31 times the maximum recommended human dose (MRHD), respectively. Roflumilast induced post-implantation loss in rats at oral doses greater than or equal to 12 times the MRHD. Roflumilast induced stillbirth and decreased pup viability in mice at oral doses 19 and 59 times the MRHD, respectively. Roflumilast has been shown to adversely affect pup post-natal development when dams were treated with an oral dose 59 times the MRHD during pregnancy and lactation periods in mice (see Data).

The background risk of major birth defects and miscarriage for the indicated population is unknown. In the U.S. general population, the estimated background risk of major birth defects and miscarriage in clinically recognized pregnancies is 2% to 4% and 15% to 20%, respectively.

Clinical Considerations

Labor or Delivery

Avoid using ZORYVE cream during labor and delivery. There are no human studies that have investigated effects of ZORYVE cream on preterm labor or labor at term; however, animal studies showed that oral roflumilast disrupted the labor and delivery process in mice.

Data

Animal Data

In an embryo-fetal development study, pregnant rats were dosed orally during the period of organogenesis with up to 1.8 mg/kg/day roflumilast (36 times the MRHD on a mg/m^2 basis). No evidence of structural abnormalities or effects on survival rates were observed. Roflumilast did not affect embryo-fetal development at a maternal oral dose of 0.2 mg/kg/day (4 times the MRHD on a mg/m^2 basis).

In a fertility and embryo-fetal development study, male rats were dosed orally with up to 1.8 mg/kg/day roflumilast for 10 weeks and females for 2 weeks prior to pairing and throughout the organogenesis period. Roflumilast induced pre- and post-implantation loss at maternal oral doses greater than or equal to 0.6 mg/kg/day (12 times the MRHD on a mg/m^2 basis). Roflumilast did not cause fetal structural abnormalities at maternal oral doses up to 1.8 mg/kg/day (35 times the MRHD on a mg/m^2 basis).

In an embryo-fetal development study in rabbits, pregnant does were dosed orally with 0.8 mg/kg/day roflumilast during the period of organogenesis. Roflumilast did not cause fetal structural abnormalities at the maternal oral doses of 0.8 mg/kg/day (31 times the MRHD on a mg/m^2 basis).

In pre- and post-natal developmental studies in mice, dams were dosed orally with up to 12 mg/kg/day roflumilast during the period of organogenesis and lactation. Roflumilast induced stillbirth and decreased pup viability at maternal oral doses greater than 2 mg/kg/day and 6 mg/kg/day, respectively (19 and 59 times the MRHD on a mg/m^2 basis, respectively). Roflumilast induced delivery retardation in pregnant mice at maternal oral doses greater than 2 mg/kg/day (19 times the MRHD on a mg/m^2 basis). Roflumilast decreased pup rearing frequencies at a maternal oral dose of 6 mg/kg/day during pregnancy and lactation (59 times the MRHD on a mg/m^2 basis). Roflumilast also decreased survival and forelimb grip reflex and delayed pinna detachment in mouse pups at a maternal oral dose of 12 mg/kg/day (116 times the MRHD on a mg/m^2 basis).

8.2 Lactation

Risk Summary

There are no data on the presence of roflumilast or its metabolite in human milk, the effects on the breastfed infant, or the effects on milk production.

Roflumilast and/or its metabolites are excreted into the milk of lactating rats (see Data). When a drug is present in animal milk, it is likely that the drug will be present in human milk. The developmental and health benefits of breastfeeding should be considered along with the mother's clinical need for ZORYVE cream and any potential adverse effects on the breastfed infant from ZORYVE cream or from the underlying maternal condition.

Clinical Considerations

To minimize potential exposure to the breastfed infant via breast milk, use ZORYVE cream on the smallest area of skin and for the shortest duration possible while breastfeeding. To avoid direct infant exposure, advise breastfeeding women not to apply ZORYVE cream directly to the nipple or areola. If applied to the patient's chest, avoid exposure via direct contact with the infant's skin.

Data

Animal Data

Roflumilast and/or its metabolite concentrations measured 8 hours after an oral dose of 1 mg/kg given to lactating rats were 0.32 and 0.02 mcg/g in the milk and pup liver, respectively. The concentration of roflumilast in animal milk does not necessarily predict the concentration of drug in human milk.

8.3 Females and Males of Reproductive Potential

Infertility

In a human spermatogenesis study, oral roflumilast 500 mcg had no effects on semen parameters or reproductive hormones during the 3-month treatment period and the following 3-month off-treatment period.

8.4 Pediatric Use

Plaque Psoriasis

The safety and effectiveness of ZORYVE cream, 0.3%, for the topical treatment of plaque psoriasis, including intertriginous areas, have been established in pediatric patients 6 years of age and older. Use of ZORYVE cream, 0.3%, in pediatric patients 6 years of age and older is supported by data from two 8-week, vehicle-controlled, safety and efficacy trials which included 18 subjects 6 to 17 years of age, of whom 11 received ZORYVE cream, 0.3%. Use of ZORYVE cream, 0.3%, in pediatric patients 12 years of age and older is also supported by data from open-label trials of 2- and 24-weeks duration which included 18 subjects 12 to 17 years of age treated with ZORYVE cream, 0.3%. Use of ZORYVE cream, 0.3%, in pediatric patients 6 to less than 12 years of age is also supported by data from one 4-week, open-label, safety and pharmacokinetic (PK) study which included 20 pediatric subjects 6 to less than 12 years of age [see Adverse Reactions (6.1), Clinical Pharmacology (12.3), Clinical Studies (14.1)].

The safety and effectiveness of ZORYVE cream, 0.3%, have not been established in pediatric patients younger than 6 years of age.

Atopic Dermatitis

ZORYVE Cream, 0.15%

The safety and effectiveness of ZORYVE cream, 0.15%, for the topical treatment of mild to moderate atopic dermatitis have been established in pediatric patients 6 years of age and older. Use of ZORYVE cream, 0.15%, in this age group is supported by data from two 4-week, vehicle-controlled, safety and efficacy trials which included 615 subjects 6 to 17 years of age, of whom 406 received ZORYVE cream, 0.15%, [see Clinical Pharmacology (12.3), Clinical Studies (14.2)]. Use of ZORYVE cream, 0.15%, in pediatric patients 6 years of age and older is also supported by data from 481 pediatric subjects treated with ZORYVE cream, 0.15%, in open-label trials, of which 104 were treated for 52 weeks.

In an open-label PK trial in 36 pediatric subjects 2 to 16 years of age, following topical administration of roflumilast cream, 0.15%, once daily for 2 weeks, mean systemic exposure of roflumilast and roflumilast N-oxide in subjects 2 to 5 years of age was approximately 3.2-fold and 5.2-fold higher, respectively, compared to subjects 12 to 16 years of age, and approximately 2-fold and 2.3-fold higher, respectively, compared to subjects 6 to 11 years of age.

The safety and effectiveness of ZORYVE cream, 0.15%, have not been established in pediatric patients younger than 6 years of age.

ZORYVE Cream, 0.05%

The safety and effectiveness of ZORYVE cream, 0.05%, for the topical treatment of mild to moderate atopic dermatitis have been established in pediatric patients 2 to 5 years of age. Use of ZORYVE cream, 0.05%, in this age group is supported by data from one 4-week, vehicle-controlled, safety and efficacy trial which included 652 subjects 2 to 5 years of age, of whom 437 received ZORYVE cream, 0.05%, [see Clinical Pharmacology (12.3), Clinical Studies (14.2)]. Use of ZORYVE cream, 0.05%, in pediatric patients 2 to 5 years of age is also supported by data from 572 pediatric subjects treated with ZORYVE cream, 0.05%, in open-label trials, of whom 353 were treated for 52 weeks.

The safety and effectiveness of ZORYVE cream, 0.05%, have not been established in pediatric patients younger than 2 years of age and older than 6 years of age.

8.5 Geriatric Use

There were 184 patients 65 years of age and older in clinical studies for plaque psoriasis and atopic dermatitis [see Clinical Studies (14.1, 14.2)].

Plaque Psoriasis

Of the 576 patients treated with ZORYVE cream, 0.3%, in the 2 controlled clinical studies for plaque psoriasis, 56 (9.7%) were 65 to 74 years of age and 21 (3.7%) were 75 years of age and older. No overall differences in safety or effectiveness were observed between these subjects and younger subjects. Other reported clinical experience has not identified differences in responses between the geriatric and younger patients, but greater sensitivity of some older individuals cannot be ruled out.

Atopic Dermatitis

Of the 885 patients treated with ZORYVE cream, 0.15%, in the 2 controlled clinical studies for atopic dermatitis, 36 (4.1%) were 65 to 74 years of age and 8 (0.9%) were 75 years of age and older. No overall differences in safety or effectiveness were observed between these subjects and younger subjects. Other reported clinical experience has not identified differences in responses between the geriatric and younger patients, but greater sensitivity of some older individuals cannot be ruled out.

8.6 Hepatic Impairment

Oral roflumilast 250 mcg once daily for 14 days was studied in subjects with hepatic impairment. The systemic exposure of roflumilast and roflumilast N-oxide were increased in subjects with moderate (Child-Pugh B) hepatic impairment. ZORYVE cream is contraindicated in patients with moderate to severe liver impairment (Child-Pugh B or C). No dosage adjustment is needed in patients with mild (Child-Pugh A) hepatic impairment [see Contraindications (4), Clinical Pharmacology (12.3)].

11 DESCRIPTION

ZORYVE (roflumilast) cream is a white to off-white cream for topical use. The active ingredient, roflumilast, is a phosphodiesterase 4 (PDE4) inhibitor.

Roflumilast is described chemically as 3-cyclopropylmethoxy-N-(3,5-dichloropyridin-4-yl)-4-(difluoromethoxy)benzamide. The empirical formula is C17H14Cl2F2N2O3, and the molecular weight is 403.21.

The structural formula is represented below:

Roflumilast is practically insoluble in water and hexane, sparingly soluble in ethanol, and freely soluble in acetone.

Each gram of cream, 0.05%, 0.15%, or 0.3%, contains 0.5 mg, 1.5 mg, or 3 mg of roflumilast, respectively, in a cream base containing ceteareth-10 phosphate, cetearyl phosphate, cetostearyl alcohol, diethylene glycol monoethyl ether, hexylene glycol, isopropyl palmitate, methylparaben, propylparaben, purified water, sodium hydroxide, and white petrolatum. Hydrochloric acid may have been added to adjust pH.

12 CLINICAL PHARMACOLOGY

12.1 Mechanism of Action

Roflumilast and its active metabolite (roflumilast N-oxide) are inhibitors of PDE4. Roflumilast and roflumilast N-oxide inhibition of PDE4 (a major cyclic 3′,5′-adenosine monophosphate [cyclic AMP] metabolizing enzyme) activity leads to accumulation of intracellular cyclic AMP. The specific mechanism(s) by which roflumilast exerts its therapeutic action is not well defined.

12.2 Pharmacodynamics

Pharmacodynamics of ZORYVE cream in the treatment of plaque psoriasis and atopic dermatitis are unknown.

12.3 Pharmacokinetics

Absorption

Following application of ZORYVE cream, the plasma concentration versus time profile was relatively flat, generally with a peak-to-trough ratio less than 2.

Plaque Psoriasis

The PK of ZORYVE cream, 0.3%, was assessed in 18 adult and 6 pediatric subjects 13 to 16 years of age with plaque psoriasis and a mean ± SD body surface area (BSA) involvement of 26.8 ± 6.80% and 13.0 ± 3.58% in adult and pediatric subjects, respectively. In this study, on average, subjects applied 3 to 6.5 g of ZORYVE cream, 0.3%, once daily for 15 days. Plasma concentrations of roflumilast and roflumilast N-oxide (see Metabolism) were quantifiable in all but two subjects at Day 15.

In adults, the mean ± SD systemic exposure (AUC0-24) was 72.7 ± 53.1 and 628 ± 648 h∙ng/mL for roflumilast and the N-oxide metabolite, respectively. In pediatric subjects (13 to 16 years of age), the mean ± SD AUC0-24 was 25.1 ± 24.0 and 140 ± 179 h∙ng/mL for roflumilast and the N-oxide metabolite, respectively.

The PK of ZORYVE cream, 0.3%, was assessed in 10 pediatric subjects (6 to less than 12 years of age) with at least mild plaque psoriasis and a mean ± SD BSA involvement of 10.9 ± 6.56%. The 14-day mean ± SD extrapolated AUC0-24 was 75.6 ± 87.3 and 693 ± 986 h∙ng/mL for roflumilast and the N-oxide metabolite, respectively. In another study, the PK of ZORYVE cream, 0.3%, was assessed in 9 pediatric subjects (2 to less than 6 years of age) with at least mild plaque psoriasis and a mean ± SD BSA involvement of 9.44 ± 5.57%. The 14-day mean ± SD extrapolated AUC0-24 was 51.6 ± 29.9 and 539 ± 372 h∙ng/mL for roflumilast and the N-oxide metabolite, respectively.

Atopic Dermatitis

The PK of ZORYVE cream, 0.15%, was assessed in 12 pediatric subjects 12 to 16 years of age and 13 pediatric subjects 6 to 11 years of age with atopic dermatitis and a mean ± SD BSA involvement of 33.7 ± 14.8% and 43.5 ± 10.5%, respectively. On average, subjects applied 8.2 to 10.5 g of ZORYVE cream, 0.15%, once daily.

In pediatric subjects 12 to 16 years of age, the Day 14 mean ± SD systemic exposure (AUC0-24) was 62.9 ± 53.0 and 336 ± 310 h∙ng/mL for roflumilast and the N-oxide metabolite, respectively. In pediatric subjects 6 to 11 years of age, the Day 14 mean ± SD AUC0-24 was 102 ± 96.5 and 743 ± 710 h∙ng/mL for roflumilast and the N-oxide metabolite, respectively.

The PK of ZORYVE cream, 0.05%, was assessed in 9 pediatric subjects 2 to 5 years of age with atopic dermatitis and a mean ± SD BSA involvement of 42.4 ± 6.21%. On average, subjects applied 5.2 g of ZORYVE cream, 0.05%, once daily.

In pediatric subjects 2 to 5 years of age, the Day 14 mean ± SD systemic exposure (AUC0-24) was 47.2 ± 27.4 and 338 ± 280 h∙ng/mL for roflumilast and the N-oxide metabolite, respectively.

Distribution

Plasma protein binding of roflumilast and its N-oxide metabolite is approximately 99% and 97%, respectively.

Elimination

The plasma clearance after short-term intravenous infusion of roflumilast is on average about 9.6 L/h. Following topical administration, the half-lives of roflumilast and the N-oxide metabolite were 4.0 and 4.6 days, respectively.

Metabolism

Roflumilast is extensively metabolized via Phase I (cytochrome P450) and Phase II (conjugation) reactions. The N-oxide metabolite is the only major metabolite observed in the plasma of humans. Following oral administration, roflumilast and roflumilast N-oxide account for the majority (87.5%) of total dose administered in plasma. Roflumilast was not detectable in urine, while roflumilast N-oxide was only a trace metabolite (less than 1%). Other conjugated metabolites such as roflumilast N-oxide glucuronide and 4-amino-3,5-dichloropyridine N-oxide were detected in urine.

While roflumilast is 3 times more potent than roflumilast N-oxide at inhibition of the PDE4 enzyme in vitro, the plasma AUC of roflumilast N-oxide on average is approximately 8-fold greater than the plasma AUC of roflumilast following topical administration. A similar ratio was observed following intravenous administration, whereas following oral administration the N-oxide metabolite circulated on average about 10-fold higher than the parent drug.

Specific Populations

Following topical administration, no clinically significant differences in the pharmacokinetics of roflumilast and roflumilast N-oxide were observed based on sex, race, or ethnicity.

Patients with Hepatic Impairment

No studies were conducted with topical roflumilast in subjects with hepatic impairment; however, oral roflumilast 250 mcg once daily for 14 days was studied in subjects with mild to moderate hepatic impairment classified as Child-Pugh A and B (8 subjects in each group). The AUC of roflumilast and roflumilast N-oxide were increased by 51% and 24%, respectively, in Child-Pugh A subjects and by 92% and 41%, respectively, in Child-Pugh B subjects, as compared to age-, weight-, and gender-matched healthy subjects. The Cmax of roflumilast and roflumilast N-oxide were increased by 3% and 26%, respectively, in Child-Pugh A subjects and by 26% and 40%, respectively, in Child-Pugh B subjects, as compared to healthy subjects [see Contraindications (4)].

Patients with Renal Impairment

No studies were conducted with topical roflumilast in subjects with renal impairment. Following oral administration in 12 subjects with severe renal impairment, no clinically significant differences in the pharmacokinetics of roflumilast and roflumilast N-oxide were observed.

Drug Interaction Studies

Clinical Studies

No formal drug-drug interaction studies were conducted with roflumilast cream.

Since a major step in roflumilast metabolism is the N-oxidation of roflumilast to roflumilast N-oxide by CYP3A4 and CYP1A2, drug interaction studies were performed with oral roflumilast and systemic inhibitors of CYP3A4 and CYP1A2 [see Drug Interactions (7.1)].

Erythromycin: In an open-label crossover study in 16 healthy volunteers, the co-administration of CYP3A4 inhibitor erythromycin (500 mg 3 times daily for 13 days) with a single oral dose of 500 mcg roflumilast resulted in 40% and 70% increase in Cmax and AUC for roflumilast, respectively, and a 34% decrease and a 4% increase in Cmax and AUC for roflumilast N-oxide, respectively.

Ketoconazole: In an open-label crossover study in 16 healthy volunteers, the co-administration of a strong CYP3A4 inhibitor ketoconazole (200 mg twice daily for 13 days) with a single oral dose of 500 mcg roflumilast resulted in 23% and 99% increase in Cmax and AUC for roflumilast, respectively, and a 38% reduction and 3% increase in Cmax and AUC for roflumilast N-oxide, respectively.

Fluvoxamine: In an open-label crossover study in 16 healthy volunteers, the co-administration of dual CYP 3A4/1A2 inhibitor fluvoxamine (50 mg daily for 14 days) with a single oral dose of 500 mcg roflumilast showed a 12% and 156% increase in roflumilast Cmax and AUC along with a 210% decrease and 52% increase in roflumilast N-oxide Cmax and AUC, respectively.

Enoxacin: In an open-label crossover study in 16 healthy volunteers, the co-administration of dual CYP 3A4/1A2 inhibitor enoxacin (400 mg twice daily for 12 days) with a single oral dose of 500 mcg roflumilast resulted in an increased Cmax and AUC of roflumilast by 20% and 56%, respectively. Roflumilast N-oxide Cmax was decreased by 14% while roflumilast N-oxide AUC was increased by 23%.

Cimetidine: In an open-label crossover study in 16 healthy volunteers, the co-administration of a dual CYP 3A4/1A2 inhibitor cimetidine (400 mg twice daily for 7 days) with a single oral dose of 500 mcg roflumilast resulted in a 46% and 85% increase in roflumilast Cmax and AUC; and a 4% decrease in Cmax and 27% increase in AUC for roflumilast N-oxide, respectively.

Oral Contraceptives Containing Gestodene and Ethinyl Estradiol: In an open-label crossover study in 20 healthy adult volunteers, co-administration of a single oral dose of roflumilast with repeated doses of a fixed combination oral contraceptive containing 0.075 mg gestodene and 0.03 mg ethinyl estradiol to steady state caused a 38% increase and 12% decrease in Cmax of roflumilast and roflumilast N-oxide, respectively. Roflumilast and roflumilast N-oxide AUCs were increased by 51% and 14%, respectively.

In Vitro Studies

Cytochrome P450 (CYP) Enzymes: In vitro studies suggest that the biotransformation of roflumilast to its N-oxide metabolite is mediated by CYP1A2 and 3A4. Based on further in vitro results in human liver microsomes, roflumilast and roflumilast N-oxide in therapeutic plasma concentrations do not inhibit CYP1A2, 2A6, 2B6, 2C8, 2C9, 2C19, 2D6, 2E1, 3A4/5, or 4A9/11; therefore, there is a low probability of relevant interactions with substances metabolized by these P450 enzymes. In addition, in vitro studies demonstrated no induction of the CYP1A2, 2A6, 2C9, 2C19, or 3A4/5 and only a weak induction of CYP2B6 by roflumilast.

13 NONCLINICAL TOXICOLOGY

13.1 Carcinogenesis, Mutagenesis, Impairment of Fertility

Long-term studies were conducted in hamsters and mice with roflumilast to evaluate its carcinogenic potential. In 2-year oral gavage carcinogenicity studies, roflumilast treatment resulted in dose-related, statistically significant increases in the incidence of undifferentiated carcinomas of nasal epithelium in hamsters at doses greater than or equal to 8 mg/kg/day (12 times the MRHD on an AUC basis). The tumorigenicity of roflumilast appears to be attributed to a reactive metabolite of 4-amino-3,5-dichloropyridine N-oxide (ADCP N-oxide). No evidence of tumorigenicity was observed in mice at roflumilast oral doses up to 12 and 18 mg/kg/day in females and males, respectively (11 and 17 times the MRHD, respectively, on an AUC basis).

In a 2-year dermal mouse carcinogenicity study, no evidence of carcinogenicity was observed at topical doses of roflumilast cream up to 1% applied at 2 mL/kg/day (4 times the MRHD on an AUC basis).

Roflumilast tested positive in an in vivo mouse micronucleus test, but negative in the following assays: the Ames test, an in vitro chromosome aberration assay in human lymphocytes, an in vitro HPRT assay with V79 cells, an in vitro micronucleus test with V79 cells, a DNA adduct formation assay in rat nasal mucosa, liver, and testes, and an in vivo mouse bone marrow chromosome aberration assay. Roflumilast N-oxide was negative in the Ames test and an in vitro micronucleus test with V79 cells.

In a fertility study, oral roflumilast decreased fertility rates in male rats at 1.8 mg/kg/day (35 times the MRHD on a mg/m^2 basis). The male rats also showed increases in the incidence of tubular atrophy, degeneration in the testis, and spermiogenic granuloma in the epididymides. No effect on rat fertility rate or male reproductive organ morphology was observed at 0.6 mg/kg/day (12 times the MRHD on a mg/m^2 basis). In a female fertility study, no effect on fertility was observed up to the highest roflumilast dose of 1.5 mg/kg/day in rats (29 times the MRHD on a mg/m^2 basis).

14 CLINICAL STUDIES

14.1 Plaque Psoriasis

Adult and Pediatric Subjects 6 Years of Age and Older

Two multicenter, randomized, double-blind, vehicle-controlled trials (DERMIS-1 [NCT04211363] and DERMIS-2 [NCT04211389]) enrolled a total of 881 adult and pediatric subjects 6 years of age or older with mild to severe plaque psoriasis. Subjects were randomized 2:1 to receive ZORYVE cream, 0.3%, or vehicle cream applied topically once daily for 8 weeks. The median age of the trial population was 47 years (range 6 to 88 years of age). The trial population was 64% male and 36% female; 82.3% were White, 7.1% Asian, 3.6% Black or African American, 0.9% Native Hawaiian or Other Pacific Islander, 0.7% American Indian or Alaska Native, 0.5% more than one race, 3.3% other races, and 1.6% with missing racial information. For ethnicity, 75.7% of subjects identified as Not Hispanic or Latino, 24.1% identified as Hispanic or Latino, and 0.2% were unknown. The median body surface area (BSA) affected of the trial population was 5.5% (range 2% to 20%). At baseline, 16% of subjects had an Investigator Global Assessment (IGA) score of 2 (mild), 76% had an IGA score of 3 (moderate), and 8% had an IGA score of 4 (severe). One hundred seventy-nine (20%) subjects had a baseline intertriginous IGA (I-IGA) score of 2 or higher (mild), and 678 (77%) subjects had a baseline Worst Itch Numeric Rating Scale (WI-NRS) score of 4 or higher on a scale of 0 to 10.

The primary endpoint was the proportion of subjects who achieved IGA treatment success at Week 8 (Table 4). Success was defined as a score of "Clear" (0) or "Almost Clear" (1), plus a 2-grade improvement from baseline.

Table 4: IGA Treatment Success [IGA treatment success was defined as an IGA score of "Clear" (0) or "Almost Clear" (1), plus a 2-grade IGA score improvement from baseline at Week 8 (Multiple Imputation).] at Week 8 in Adult and Pediatric Subjects 6 Years of Age and Older with Mild to Severe Plaque Psoriasis in Trials DERMIS-1 and DERMIS-2
 | DERMIS-1 |  | DERMIS-2
 | ZORYVE Cream, 0.3% | Vehicle Cream | ZORYVE Cream, 0.3% | Vehicle Cream
Subjects randomized | N=286 | N=153 | N=290 | N=152
IGA success | 41.5% | 5.8% | 36.7% | 7.1%
Difference from vehicle (95% CI) [Treatment difference and 95% CI are based on the CMH method stratified by site, baseline IGA, and baseline intertriginous involvement.] | 39.7% (32.4%, 47.0%) |  | 29.5% (21.5%, 37.6%)
Abbreviations: CI = Confidence Interval

Secondary endpoints included the proportion of subjects that achieved I-IGA success at Week 8 and WI-NRS success sequentially at Weeks 8, 4, and 2 (see Figure 1). WI-NRS success was defined as a reduction of at least 4 points from baseline in subjects with a baseline WI-NRS score of at least 4.

Figure 1: WI-NRS Success [WI-NRS success is a reduction of at least 4 points in subjects with a WI-NRS score of 4 or higher at baseline.] Over Time in Adult and Pediatric Subjects 12 Years of Age and Older with Mild to Severe Plaque Psoriasis in Trials DERMIS-1 and DERMIS-2

†The treatment difference at Week 2 in DERMIS-1 was not statistically significant.

Among subjects with an I-IGA score of at least 2 (mild) at baseline (approximately 22% of subjects in DERMIS-1 and 19% in DERMIS-2), there was a higher percentage of subjects who achieved I-IGA success at Week 8 in the group who received ZORYVE cream, 0.3%, compared to the group who received vehicle cream (DERMIS-1: 71.5% vs. 13.8%; DERMIS-2: 67.5% vs. 17.4%).

14.2 Atopic Dermatitis

Adult and Pediatric Subjects 6 Years of Age and Older

Two multicenter, randomized, double-blind, vehicle-controlled trials (INTEGUMENT-1 [NCT04773587] and INTEGUMENT-2 [NCT04773600]) enrolled a total of 1337 adult and pediatric subjects 6 years of age and older (615 subjects were 6 to 17 years of age) with mild to moderate atopic dermatitis. Subjects were randomized 2:1 to receive ZORYVE cream, 0.15%, or vehicle cream applied once daily for 4 weeks. The median age of the trial population was 20 years (range 6 to 91 years of age). The trial population was 57% female; 59.5% were White, 20.3% Black or African American, 13.2% Asian, 3.4% other races, 2.8% more than one race, 0.6% American Indian or Alaska Native, and 0.1% Native Hawaiian or Other Pacific Islander. For ethnicity, 82.8% of subjects identified as Not Hispanic or Latino, 16.6% identified as Hispanic or Latino, and 0.6% were unknown. At baseline, subjects had a mean affected BSA of 14% (range of 3% to 88%), and 42% had facial involvement. At baseline, 24% of subjects had a validated Investigator Global Assessment for Atopic Dermatitis (vIGA-AD) score of 2 (mild), and 76% had a vIGA-AD score of 3 (moderate). Eight hundred thirteen (60.8%) subjects 12 years of age and older had a baseline WI-NRS score of 4 or higher on a scale of 0 to 10.

The primary endpoint was the proportion of subjects who achieved vIGA-AD treatment success at Week 4 (Table 5). Success was defined as a score of "Clear" (0) or "Almost Clear" (1), plus a 2-grade improvement from baseline.

Secondary endpoints included the proportion of subjects that achieved vIGA-AD success at Weeks 2 and 1 (Figure 2) and WI-NRS success at Weeks 4, 2, and 1 (Table 6, Figure 3). WI-NRS success was defined as a reduction of at least 4 points from baseline in subjects 12 years of age or older with a baseline WI-NRS score of at least 4.

Table 5: vIGA-AD Success [vIGA-AD success was defined as a vIGA-AD score of "Clear" (0) or "Almost Clear" (1), plus a 2-grade vIGA-AD score improvement from baseline at Week 4 (Multiple Imputation).] at Week 4 in Adult and Pediatric Subjects 6 Years of Age and Older with Mild to Moderate Atopic Dermatitis in Trials INTEGUMENT-1 and INTEGUMENT-2
 | INTEGUMENT-1 |  | INTEGUMENT-2
 | ZORYVE Cream, 0.15% | Vehicle Cream | ZORYVE Cream, 0.15% | Vehicle Cream
Subjects randomized | N=433 | N=221 | N=451 | N=232
vIGA-AD success | 32.0% | 15.2% | 28.9% | 12.0%
Difference from vehicle (95% CI) [The difference in percent and related 95% CIs are Mantel-Haenszel estimates stratified by pooled study site and vIGA-AD randomization strata.] | 17.4% (11.09%, 23.75%) |  | 16.5% (10.61%, 22.42%)
Abbreviations: CI = Confidence Interval

Figure 2: vIGA-AD Success [vIGA-AD success was defined as a vIGA-AD score of "Clear" (0) or "Almost Clear" (1), plus a 2-grade vIGA-AD score improvement from baseline at Week 4 (Multiple Imputation).] Over Time in Adult and Pediatric Subjects 6 Years of Age and Older with Mild to Moderate Atopic Dermatitis in Trials INTEGUMENT-1 and INTEGUMENT-2

†The treatment difference at Week 1 in INTEGUMENT-2 was not statistically significant.

Table 6: WI-NRS Success [WI-NRS success was defined as a reduction of at least 4 points from baseline for subjects 12 years of age or older with a baseline score of at least 4.] at Week 4 in Adult and Pediatric Subjects 12 Years of Age and Older with Mild to Moderate Atopic Dermatitis in Trials INTEGUMENT-1 and INTEGUMENT-2
 | INTEGUMENT-1 |  | INTEGUMENT-2
 | ZORYVE Cream, 0.15% | Vehicle Cream | ZORYVE Cream, 0.15% | Vehicle Cream
Subjects randomized | N=433 | N=221 | N=451 | N=232
Subjects ≥12 years randomized with baseline WI-NRS ≥4 | N=278 | N=135 | N=264 | N=136
WI-NRS success | 33.6% | 20.7% | 30.2% | 12.4%
Difference from vehicle (95% CI) [The difference in percent and related 95% CIs are Mantel-Haenszel estimates stratified by pooled study site and vIGA-AD randomization strata.] | 13.3% (4.01%, 22.60%) |  | 15.0% (6.52%, 23.54%)
Abbreviations: CI = Confidence Interval

Figure 3: WI-NRS Success [WI-NRS success in subjects 12 years of age or older is a reduction of at least 4 points in subjects with a WI-NRS score of 4 or higher at baseline.] Over Time in Adult and Pediatric Subjects 12 Years of Age and Older with Mild to Moderate Atopic Dermatitis in Trials INTEGUMENT-1 and INTEGUMENT-2

Pediatric Subjects 2 to 5 Years of Age

A multicenter, randomized, double-blind, vehicle-controlled trial (INTEGUMENT-PED [NCT04845620]) enrolled a total of 652 pediatric subjects 2 to 5 years of age with mild to moderate atopic dermatitis. Subjects were randomized 2:1 to receive ZORYVE cream, 0.05%, or vehicle cream applied once daily for 4 weeks. The median age of the trial population was 3 years (range 2 to 5 years of age). The trial population was 52% male; 69.1% were White, 15.4% Black or African American, 8.3% Asian, 1.8% other races, 4.9% more than one race, and 0.5% American Indian or Alaska Native. For ethnicity, 82.2% of subjects identified as Not Hispanic or Latino, 17.4% identified as Hispanic or Latino, and 0.5% were unknown. At baseline, subjects had a mean affected BSA of 22% (range of 3% to 82%), and 53% had facial involvement. At baseline, 22% of subjects had a validated Investigator Global Assessment for Atopic Dermatitis (vIGA-AD) score of 2 (mild), and 78% had a vIGA-AD score of 3 (moderate).

The primary endpoint was the proportion of subjects who achieved vIGA-AD treatment success at Week 4 (Table 7). Success was defined as a score of "Clear" (0) or "Almost Clear" (1), plus a 2-grade improvement from baseline. Secondary endpoints included the proportion of subjects that achieved vIGA-AD success at Weeks 1 and 2 (Figure 4).

Table 7: vIGA-AD Success [vIGA-AD success was defined as a vIGA-AD score of "Clear" (0) or "Almost Clear" (1), plus a 2-grade vIGA-AD score improvement from baseline at Week 4 (Multiple Imputation).] at Week 4 in Pediatric Subjects 2 to 5 Years of Age with Mild to Moderate Atopic Dermatitis in Trial INTEGUMENT-PED
 | INTEGUMENT-PED
 | ZORYVE Cream, 0.05% | Vehicle Cream
Subjects randomized | N=436 | N=215
vIGA-AD success | 25.4% | 10.7%
Difference from vehicle (95% CI) [The difference in percent and related 95% CIs are Mantel-Haenszel estimates stratified by pooled study site and vIGA-AD randomization strata.] | 14.9% (9.04%, 20.79%)
Abbreviations: CI = Confidence Interval

Figure 4: vIGA-AD Success [vIGA-AD success was defined as a vIGA-AD score of "Clear" (0) or "Almost Clear" (1), plus a 2-grade vIGA-AD score improvement from baseline at Week 4 (Multiple Imputation).] Over Time in Pediatric Subjects 2 to 5 Years of Age with Mild to Moderate Atopic Dermatitis in Trial INTEGUMENT-PED

16 HOW SUPPLIED/STORAGE AND HANDLING

How Supplied

ZORYVE (roflumilast) cream is a white to off-white cream supplied as follows:

- Cream, 0.3%: 3 mg of roflumilast per gram supplied in 60-gram aluminum tubes (NDC 80610-130-60).
- Cream, 0.15%: 1.5 mg of roflumilast per gram supplied in 60-gram aluminum tubes (NDC 80610-115-60).
- Cream, 0.05%: 0.5 mg of roflumilast per gram supplied in 60-gram aluminum tubes (NDC 80610-105-60).

Storage and Handling

Store at 20°C to 25°C (68°F to 77°F); excursions permitted between 15°C and 30°C (59°F and 86°F). [See USP Controlled Room Temperature]

17 PATIENT COUNSELING INFORMATION

Advise the patient or caregiver to read the FDA-approved patient labeling (Patient Information).

Administration Instructions

Advise patients or caregivers that ZORYVE cream is for topical use only and is not for ophthalmic, oral, or intravaginal use.

Instruct patients and caregivers to wash hands after applying ZORYVE cream.

Lactation

Advise the patient to use ZORYVE cream on the smallest area of skin and for the shortest duration possible while breastfeeding. Instruct the patient who is breastfeeding not to apply ZORYVE cream directly to the nipple or areola to avoid direct infant exposure. Instruct the patient to avoid inadvertent contact of treated areas with infant skin [see Use in Specific Populations (8.2)].

Marketed by: Arcutis Biotherapeutics, Inc.
Westlake Village, CA 91361
For more information, call 1-805-418-5006 or visit http://www.zoryve.com.

© 2025 Arcutis Biotherapeutics, Inc. All rights reserved.

V6

Patient Information
ZORYVE® (zor-EEV)
(roflumilast) cream

Important information: ZORYVE cream is for use on the skin (topical use) only. Do not use ZORYVE cream in or on your eyes, mouth, or vagina.

What is ZORYVE cream?

- ZORYVE cream 0.3% is a prescription medicine used on the skin (topical), including in areas with skin folds, to treat plaque psoriasis in adults and children 6 years of age and older.
  It is not known if ZORYVE cream 0.3% is safe and effective in children with plaque psoriasis under 6 years of age.
- ZORYVE cream 0.15% is a prescription medicine used on the skin (topical) to treat mild to moderate eczema (atopic dermatitis) in adults and children 6 years of age and older.
  It is not known if ZORYVE cream 0.15% is safe and effective in children with mild to moderate eczema (atopic dermatitis) under 6 years of age.
- ZORYVE cream 0.05% is a prescription medicine used on the skin (topical) to treat mild to moderate eczema (atopic dermatitis) in children 2 to 5 years of age.
  It is not known if ZORYVE cream 0.05% is safe and effective in children with mild to moderate eczema (atopic dermatitis) under 2 years of age and 6 years of age and older.

Do not use ZORYVE cream if you have certain liver problems.

Before using ZORYVE cream, tell your healthcare provider about all of your medical conditions, including if you:

- have liver problems.
- are pregnant or plan to become pregnant. It is not known if ZORYVE cream will harm your unborn baby.
- are breastfeeding or plan to breastfeed. It is not known if ZORYVE cream passes into your breast milk. Talk to your healthcare provider about the best way to feed your baby during treatment with ZORYVE cream.
  Breastfeeding women using ZORYVE cream should use it on the smallest area of the skin and for the shortest time needed. Do not apply ZORYVE cream directly to the nipple or areola to avoid contact with your baby.

Tell your healthcare provider about the medicines you take, including prescription and over-the-counter medicines, vitamins, and herbal supplements.

How should I use ZORYVE cream?

- Use ZORYVE cream exactly as your healthcare provider tells you to use it.
- Apply ZORYVE cream to the affected areas 1 time a day. Rub the cream in completely until you no longer see it on your skin.
- Wash your hands after applying ZORYVE cream. If someone else applies ZORYVE cream for you, they should wash their hands after applying it.

What are the possible side effects of ZORYVE cream?
The most common side effects of ZORYVE cream 0.3% in adults and children 6 years of age and older treated for plaque psoriasis include:

- diarrhea
- headache
- trouble sleeping
- nausea

- application site pain
- upper respiratory tract infections
- urinary tract infections (UTIs)

The most common side effects of ZORYVE cream 0.15% in adults and children 6 years of age and older treated for atopic dermatitis include:

- headache
- nausea
- application site pain

- diarrhea
- vomiting

The most common side effects of ZORYVE cream 0.05% in children 2 to 5 years of age treated for atopic dermatitis include:

- upper respiratory tract infections
- diarrhea
- vomiting

- stuffy or runny nose
- red or swollen eyes (like "pink eye")
- headache

These are not all of the possible side effects of ZORYVE cream.
Call your doctor for medical advice about side effects. You may report side effects to FDA at 1-800-FDA-1088.
You may also report side effects to Arcutis Biotherapeutics, Inc. by calling 1-844-692-6729.

How should I store ZORYVE cream?

- Store ZORYVE cream at room temperature from 68°F to 77°F (20°C to 25°C).

Keep ZORYVE cream and all medicines out of the reach of children.

General information about the safe and effective use of ZORYVE cream.
Medicines are sometimes prescribed for purposes other than those listed in a Patient Information leaflet. Do not use ZORYVE cream for a condition for which it was not prescribed. Do not give ZORYVE cream to other people, even if they have the same symptoms you have. It may harm them. You can ask your healthcare provider or pharmacist for information about ZORYVE cream that is written for health professionals.

What are the ingredients in ZORYVE cream?
Active ingredient: roflumilast
Inactive ingredients: ceteareth-10 phosphate, cetearyl phosphate, cetostearyl alcohol, diethylene glycol monoethyl ether, hexylene glycol, isopropyl palmitate, methylparaben, propylparaben, purified water, sodium hydroxide, and white petrolatum. Hydrochloric acid may have been added to adjust pH.
Marketed by: Arcutis Biotherapeutics, Inc.
Westlake Village, CA 91361
For more information, call 1-844-692-6729 or visit http://www.zoryve.com.

This Patient Information has been approved by the U.S. Food and Drug Administration.

Revised: 10/2025

v4

PRINCIPAL DISPLAY PANEL - 60 g Tube Carton - NDC 80610-130-60

NDC 80610-130-60

ZORYVE®
(roflumilast) cream 0.3%

For Topical Use Only
Not for oral, ophthalmic, or intravaginal use

Rx Only
Net Wt. 60 g

ARCUTIS®

PRINCIPAL DISPLAY PANEL - 60 g Tube Carton - NDC 80610-115-60

NDC 80610-115-60

ZORYVE®
(roflumilast) cream 0.15%

For Topical Use Only
Not for oral, ophthalmic, or intravaginal use

Rx Only
Net Wt. 60 g

ARCUTIS®

PRINCIPAL DISPLAY PANEL - 60 g Tube Carton - NDC 80610-105-60

NDC 80610-105-60

ZORYVE®
(roflumilast) cream 0.05%

For Topical Use Only
Not for oral, ophthalmic, or intravaginal use

Rx Only
Net Wt. 60 g

ARCUTIS®